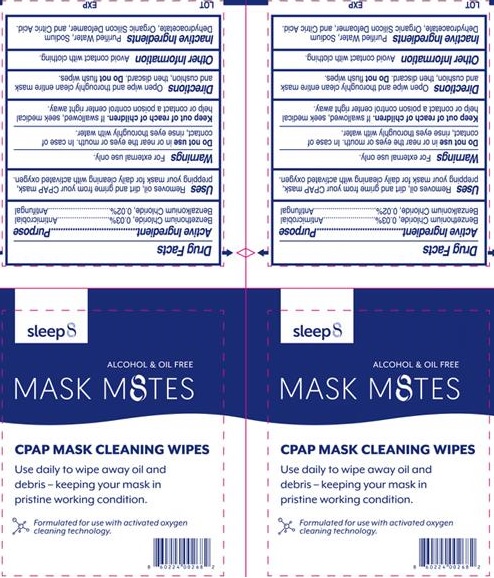 DRUG LABEL: CPAP Mask cleaning wipes
NDC: 71734-212 | Form: CLOTH
Manufacturer: JIANGMEN SHUIZIRUN SANITARY ARTICLES CO., LTD.
Category: otc | Type: HUMAN OTC DRUG LABEL
Date: 20190607

ACTIVE INGREDIENTS: BENZETHONIUM CHLORIDE 0.03 g/1 g; BENZALKONIUM CHLORIDE 0.02 g/1 g
INACTIVE INGREDIENTS: Water; SODIUM DEHYDROACETATE; CITRIC ACID MONOHYDRATE

DRUG FACTS

Active Ingredient

Benzethonium Chloride 0.03%

Benzalkonium Chloride 0.02%

Purpose

Antiseptic and antifungal

Uses:

Removes oil ,dirt and grime from your CPAP mask,prepping your mask for daily cleaning with activated oxygen.

WARNINGS

For external use only.

- for external use only.
- do not use in eyes. If this occurs, rinse thoroughly with water.
- Stop use and ask a doctor if irritation o redness develops and persists for more than 72 hours.

Keep out of reach of children.

if swallowed get medical help or contact a Poison Control Center right away.

Directions

Removes oil ,dirt and grime from your CPAP mask,prepping your mask for daily cleaning with activated oxygen.

Inactive Ingredients:

Purified water, Sodium Dehydroacetate, Organic Silicon Defoamer, Citric Acid